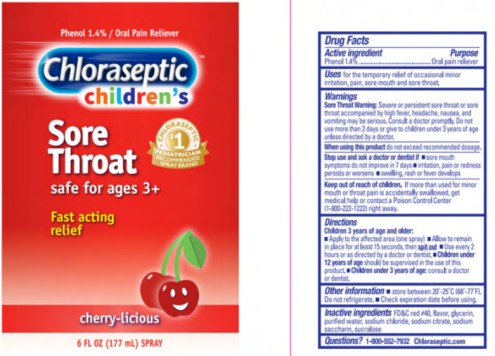 DRUG LABEL: Chloraseptic Childrens Sore Throat Cherry
NDC: 67172-930 | Form: SPRAY
Manufacturer: Prestige Brands Holdings, Inc.
Category: otc | Type: HUMAN OTC DRUG LABEL
Date: 20251023

ACTIVE INGREDIENTS: PHENOL 1.4 g/100 mL
INACTIVE INGREDIENTS: FD&C RED NO. 40; GLYCERIN; WATER; SODIUM CHLORIDE; SODIUM CITRATE, UNSPECIFIED FORM; SACCHARIN SODIUM; SUCRALOSE

Chloraseptic Childrens Sore Throat Spray Cherry

Drug Facts_________________________________________________

Active ingredient

Phenol 1.4%

Purpose

Oral pain reliever

Uses

for the temporary relief of occasional minor irritation, pain, sore mouth and sore throat.

Warnings

Sore Throat Warning: Severe or persistent sore throat or sore throat accompanied by high fever, headache, nausea, and vomiting may be serious. Consult a doctor promptly. Do not use more than 2 days or give to children under 3 years of age unless directed by a doctor.

When using this product,

do not exceed recommended dose.

Stop use and ask a doctor or dentist if

- sore mouth symptoms do not improve in 7 days
- irritation, pain or redness persists or worsens
- swelling, rash or fever develops

Keep out of reach of children.

If more than used for minor mouth or throat pain is accidentally swallowed, get medical help or contact a Poison Control Center (1-800-222-1222) right away.

Directions

- Adults and children 3years of age and older:
- Apply to the affected area (one spray)
- Allow to remain in place for at least 15 seconds, then spit out
- Use every 2 hours or as directed by a doctor or dentist
- Children under 12 years of age should be supervised in the use of this product
- Children under 3 years of age, consult a doctor or dentist

Other information

- store between 20°-25°C (68°- 77°F)
- do not refrigerate
- Check expiration date before using

Inactive ingredients

FD&C red #40, flavor, glycerin, purified water, sodium chloride, sodium citrate, sodium saccharin , sucralose

Principal Display Panel

Chloraseptic
children’s
Sore Throat
6 FL OZ (177 mL) SPRAY